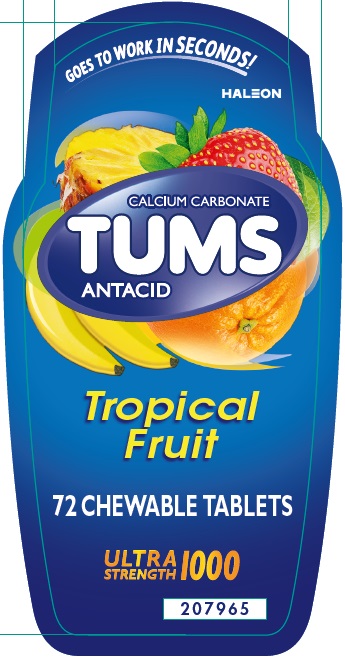 DRUG LABEL: Tums
NDC: 0135-0553 | Form: TABLET, CHEWABLE
Manufacturer: Haleon US Holdings LLC
Category: otc | Type: HUMAN OTC DRUG LABEL
Date: 20250226

ACTIVE INGREDIENTS: CALCIUM CARBONATE 1000 mg/1 1
INACTIVE INGREDIENTS: STARCH, CORN; CROSPOVIDONE, UNSPECIFIED; DEXTROSE, UNSPECIFIED FORM; FD&C RED NO. 40; ALUMINUM OXIDE; FD&C YELLOW NO. 5 ALUMINUM LAKE; FD&C YELLOW NO. 6; MAGNESIUM STEARATE; MALTODEXTRIN; SUCROSE; TALC

Drug Facts

Active ingredient (per tablet)

Calcium carbonate 1000 mg

Purpose

Antacid

Uses

relieves

- heartburn
- acid indigestion
- sour stomach
- upset stomach associated with these symptoms

Warnings

Ask a doctor or pharmacist before use if you are presently taking a prescription drug. Antacids may interact with certain prescription drugs.

When using this product

- do not take more than 7 tablets in 24 hours
- if pregnant do not take more than 5 tablets in 24 hours
- do not use the maximum dosage for more than 2 weeks, except under the advice and supervision of a doctor

Directions

- adults and children 12 years of age and over: chew 2-3 tablets as symptoms occur, or as directed by a doctor. Chew or crush tablets completely before swallowing.
- do not take for symptoms that persist for more than 2 weeks unless advised by a doctor

Other information

- each tablet contains: elemental calcium 400 mg, magnesium 10 mg
- store below 30°C (86°F)
- contains FD&C Yellow No. 5 (tartrazine) as a color additive

Inactive ingredients

corn starch, crospovidone, dextrose, FD&C red #40 lake, FD&C yellow #5 (tartrazine) lake, FD&C yellow #6 lake, flavors, magnesium stearate, maltodextrin, sucrose, talc

Questions?

1-800-897-7535

Additional Information

Safety sealed – Do not use if printed inner seal beneath cap is missing or broken.

Gluten-Free

Principal Display Panel

GOES TO WORK IN SECONDS!

CALCIUM CARBONATE
TUMS
ANTACID

Tropical
Fruit

72 CHEWABLE TABLETS

ULTRA
STRENGTH 1000